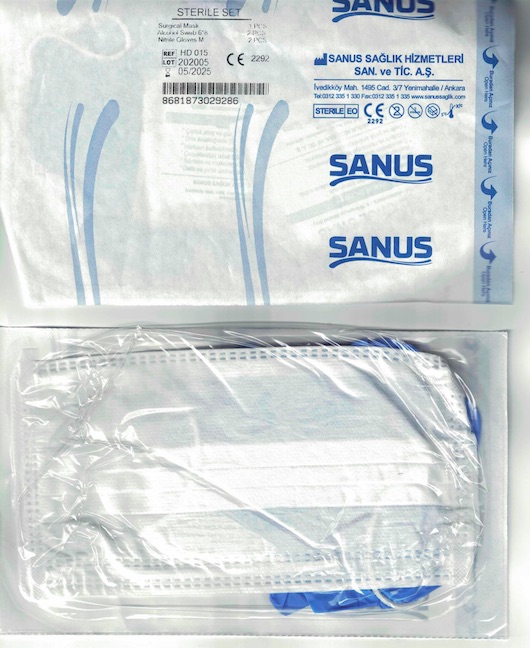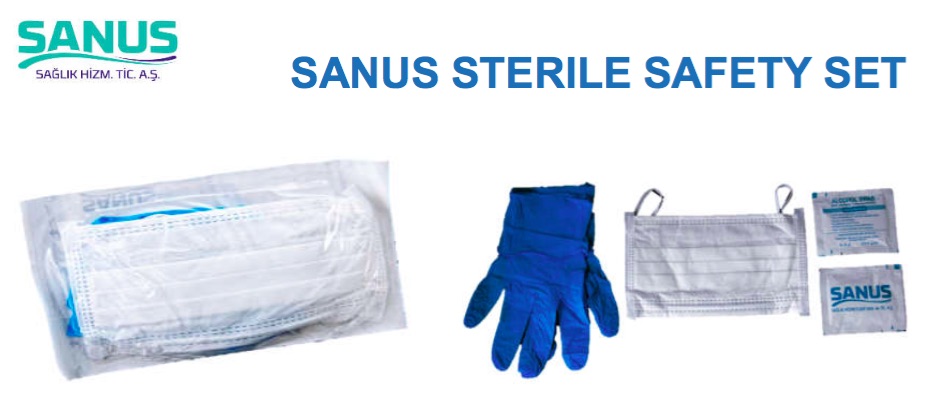 DRUG LABEL: Sanus Sterile Safety Set
NDC: 79764-000 | Form: KIT | Route: TOPICAL
Manufacturer: SANUS SAGLIK HIZMETLERI SANAYI VE TICARET ANONIM SIRKETI
Category: otc | Type: HUMAN OTC DRUG LABEL
Date: 20200728

ACTIVE INGREDIENTS: ISOPROPYL ALCOHOL 70 mL/100 mL
INACTIVE INGREDIENTS: POLYPROPYLENE (30000 MW) 66 1/100 1; ACRYLONITRILE 100 1/100 1; WATER

Sanus Sterile Safety Set

Active Ingredient

70% Isopropyl Alcohol in swab(wipe).

Directions (Swab)

Wet hands thoroughly with product and allow to dry. When finished, discard wipe in trash receptacle. Do not flush. Supervise children under 6 years of age when using this product to avoid swallowing.

Warnings

Flammable. Keep away from heat or flame.

Inactive Ingredients

Purified water USP.

Keep out of reach of children

If swallowed, get medical help or contact a Poison Control Center right away.

Purpose (Swab)

Antiseptic Cleanser

Sterile Set

Surgical Mask 1 PCS

Alcohol Swab 6*8: 2 PCS

Nitrile Glove M: 2 PCS